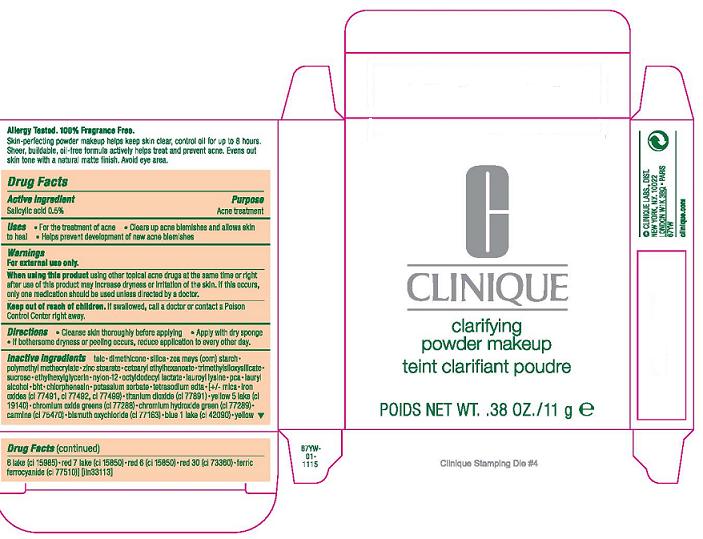 DRUG LABEL: CLINIQUE
NDC: 49527-006 | Form: POWDER
Manufacturer: CLINIQUE LABORATORIES INC
Category: otc | Type: HUMAN OTC DRUG LABEL
Date: 20110120

ACTIVE INGREDIENTS: SALICYLIC ACID 0.5 g/100 g
INACTIVE INGREDIENTS: TALC; DIMETHICONE; STARCH, CORN; ZINC STEARATE; SUCROSE; BUTYLATED HYDROXYTOLUENE

ACTIVE INGREDIENT: SALICYLIC ACID 0.5%

PURPOSE: ACNE TREATMENT

USE: FOR THE TREATMENT OF ACNE

CLEARS UP ACNE BLEMISHES AND ALLOWS SKIN TO HEAL

HELPS PREVENT DEVELOPMENT OF NEW ACNE BLEMISHES

INDICATIONS: FOR THE TREATMENT OF ACNE

WARNINGS: FOR EXTERNAL USE ONLY.

WHEN USING THIS PRODUCT: USING OTHER TOPICAL ACNE DRUGS AT THE SAME TIME OR RIGHT AFTER USE OF THIS PRODUCT MAY INCREASE DRYNESS OR IRRITATION OF THE SKIN. IF THIS OCCURS, ONLY ONE MEDICATION SHOULD BE USED UNLESS DIRECTED BY A DOCTOR.

KEEP OUT OF REACH OF CHILDREN. IF SWALLOWED, GET MEDICAL HELP OR CONTACT A POISON CONTROL CENTER RIGHT AWAY.

DIRECTIONS

- CLEANSE SKIN THOROUGHLY BEFORE APPLYING
- COVER THE ENTIRE AFFECTED AREA WITH ONE APPLICATION
- GRADUALLY INCREASE TO 2 OR 3 TIMES DAILY IF NEEDED OR AS DIRECTED BY A DOCTOR
- IF BOTHERSOME DRYNESS OR PEELING OCCURS, REDUCE APPLICATION TO EVERY OTHER DAY.

INACTIVE INGREDIENTS:
talc [] dimethicone [] silica [] zea mays (corn) starch [] polymethyl methacrylate [] zinc stearate [] cetearyl ethylhexanoate [] trimethylsiloxysilicate [] sucrose [] ethylhexylglycerin [] nylon-12 [] octyldodecyl lactate [] lauroyl lysine [] pca [] lauryl alcohol [] bht [] chlorphenesin [] potassium sorbate [] tetrasodium edta [] [+/- mica [] iron oxides (ci 77491, ci 77492, ci 77499) [] titanium dioxide (ci 77891) [] yellow 5 lake (ci 19140) [] chromium oxide greens (ci 77288) [] chromium hydroxide green (ci 77289) [] carmine (ci 75470) [] bismuth oxychloride (ci 77163) [] blue 1 lake (ci 42090) [] yellow 6 lake (ci 15985) [] red 7 lake (ci 15850) [] red 6 (ci 15850) [] red 30 (ci 73360) [] ferric ferrocyanide (ci 77510

PACKAGE LABEL

PRINCIPLE DISPLAY PANEL:
CLINIQUE
CLARIFYING POWDER MAKEUP
NET WT. .38 OZ/11 g
clinique labs dist
new york, ny 10022